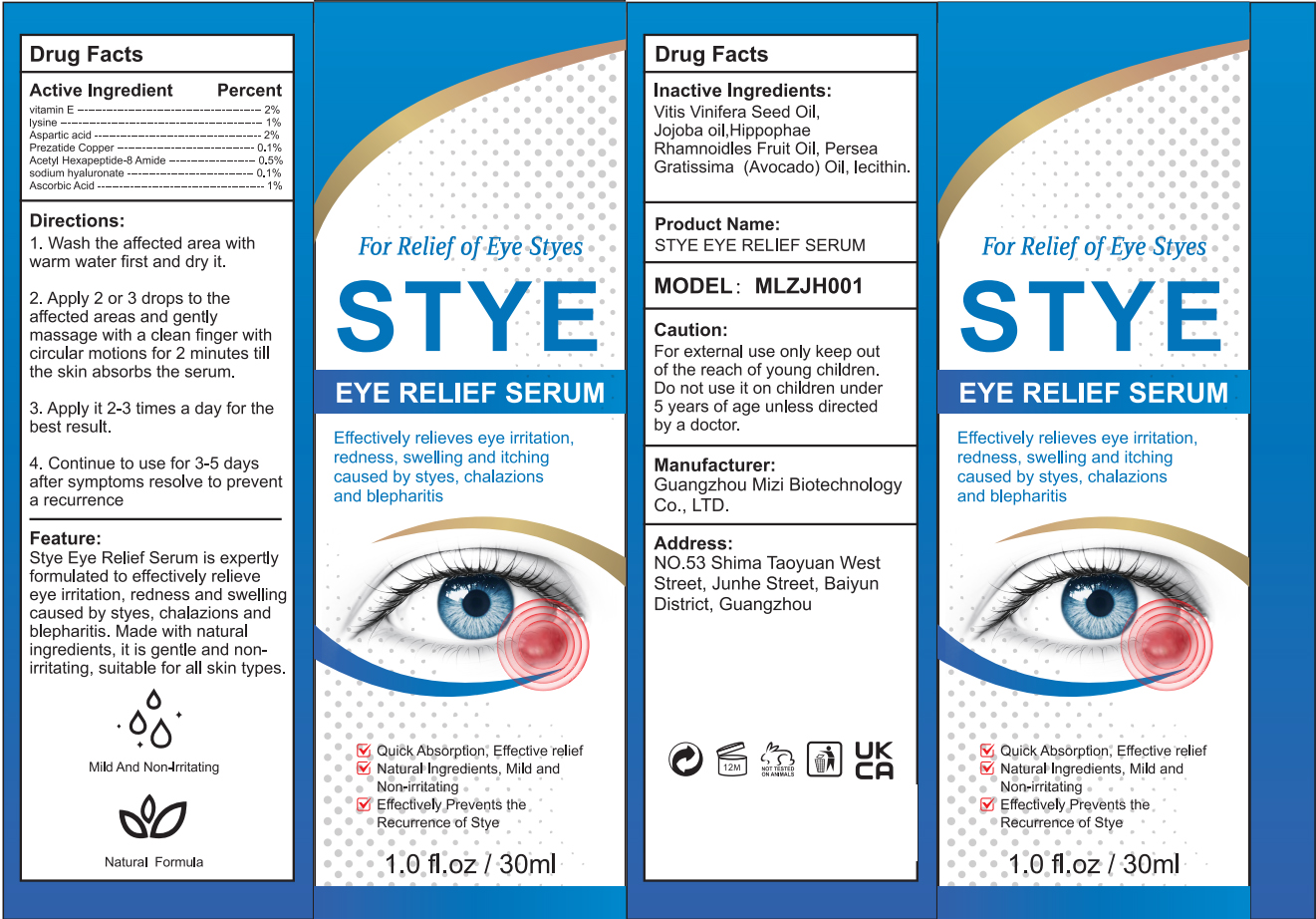 DRUG LABEL: STYE EYE RELIEF SERUM
NDC: 84896-001 | Form: PASTE
Manufacturer: Guangzhou Mizi Biotechnology Co., LTD.
Category: otc | Type: HUMAN OTC DRUG LABEL
Date: 20251217

ACTIVE INGREDIENTS: ACETYL HEXAPEPTIDE-8 AMIDE 0.5 g/100 mL; ASCORBIC ACID 1 g/100 mL; PREZATIDE COPPER 0.1 g/100 mL; ASPARTIC ACID 2 g/100 mL; LYSINE 1 g/100 mL
INACTIVE INGREDIENTS: LECITHIN, SOYBEAN; HELICHRYSUM ANGUSTIFOLIUM FLOWER OIL; AVOCADO OIL; VITAMIN E POLYETHYLENE GLYCOL SUCCINATE; SODIUM HYALURONATE; HIPPOPHAE RHAMNOIDES FRUIT OIL; GRAPE SEED OIL

84896-001 STYE EYE RELIEF SERUM

ACTIVE INGREDIENT

Vitamin E
lysine
Aspartic acid
Prezatide Copper
Acetyl Hexapeptide-8 Amide
sodium hyaluronate
ASCORBIC ACID

PURPOSE

EYE RELIEF SERUM

INDICATIONS AND USAGE

Effectively relieves eye irritation,redness, swelling and itchingcaused by styes, chalazionsand blepharitis

WARNINGS

For external use only keep outof the reach of young children.Do not use it on children under5 years of age unless directedby a doctor.

keep outof the reach of young children.

Do not use it on children under 5 years of age unless directedby a doctor.

DOSAGE AND ADMINISTRATION

1. Wash the affected area withwarm water first and dry it.
2. Apply 2 or 3 drops to theaffected areas and gentlymassage with a clean finger withcircular motions for 2 minutes tillthe skin absorbs the serum.
3. Apply it 2-3 times a day for thebest result.
4. Continue to use for 3-5 daysafter symptoms resolve to preventa recurrence

INACTIVE INGREDIENT

GRAPE SEED OIL
Jojoba oil
HIPPOPHAE RHAMNOIDES FRUIT OIL
AVOCADO OIL
SOYBEAN LECITHIN